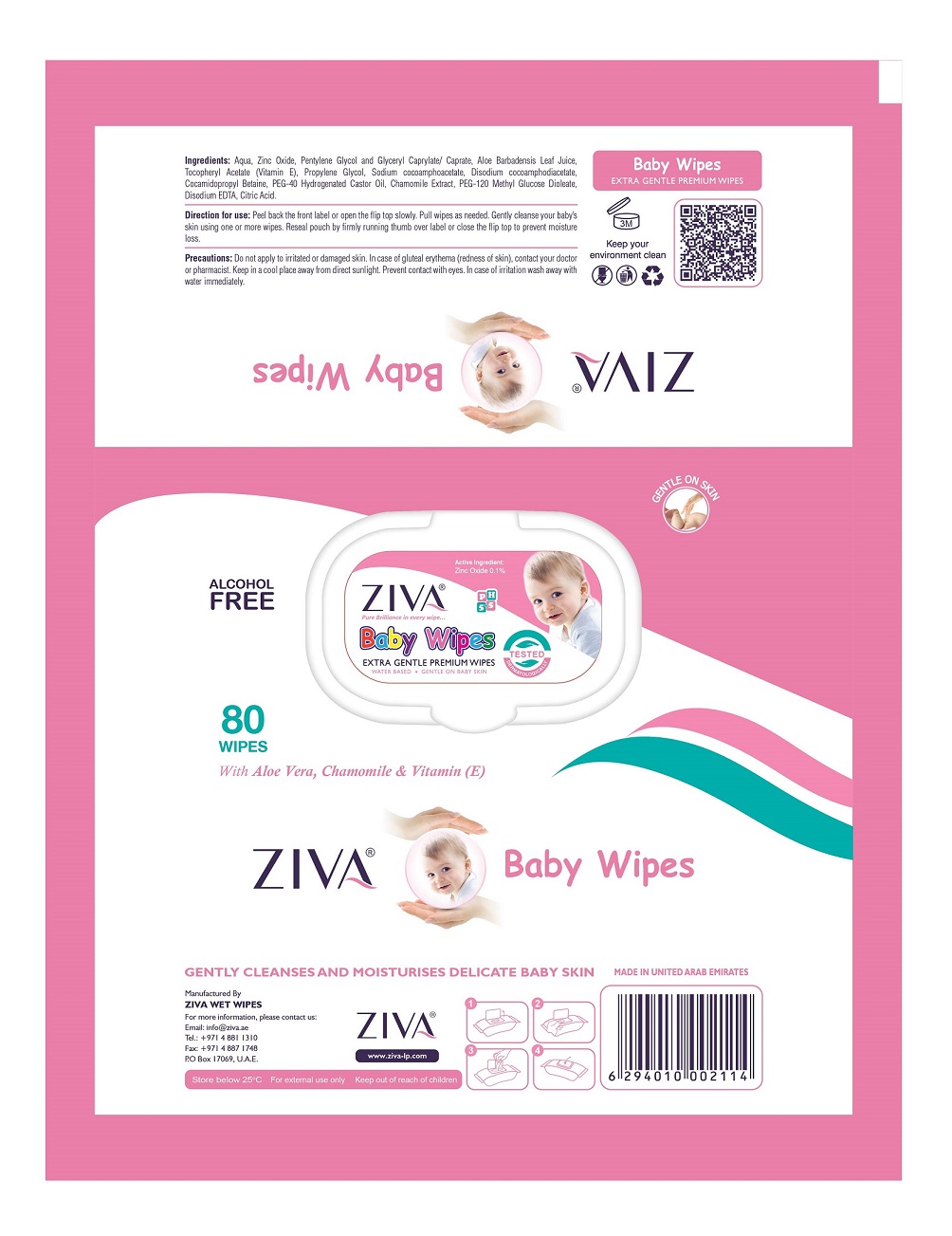 DRUG LABEL: ZIVA BABY WIPES
NDC: 81450-005 | Form: CLOTH
Manufacturer: Ziva Wetwipes FZCo
Category: otc | Type: HUMAN OTC DRUG LABEL
Date: 20231005

ACTIVE INGREDIENTS: ZINC OXIDE 0.1 g/100 mL
INACTIVE INGREDIENTS: PENTYLENE GLYCOL; WATER; GLYCERYL CAPRYLATE/CAPRATE; ALOE VERA LEAF; PROPYLENE GLYCOL; HYDROGENATED CASTOR OIL; CHAMOMILE; SODIUM COCOAMPHOACETATE; .ALPHA.-TOCOPHEROL ACETATE; CITRIC ACID MONOHYDRATE; DISODIUM COCOAMPHODIACETATE; COCAMIDOPROPYL BETAINE; METHYL GLUCOSE DIOLEATE; EDETATE DISODIUM

Drug Facts

Active Ingredient:

Zinc Oxide 0.1%

Direction for use

Peel back the front label or open the flip top slowly. Pull wipes as needed. Gently cleanse your baby's skin using one or more wipes. Reseal pouch by firmly running thumb over label to close the flip top to prevent moisture loss.

Precautions:

For external use only. Do not apply to irritated or damaged skin. In case of gluteal erythema (redness of skin), contact your doctor or pharmacist. Keep in a cool place away from direct sunlight. Prevent contact with eyes. In case of irritation wash away with water immediately.

Store below 25°C

Ingredients:

Aqua, Zinc Oxide, Pentylene Glycol and Glyceryl Caprylate / Caprate, Aloe Barbadensis Leaf Juice, Tocopheryl Acetate (Vitamin E), Propylene Glycol, Sodium cocoamphoacetate, Disodium cocoamphodiacetate, Cocamidoproply Betaine, PEG 40 Hydrogenated Castor Oil, Chamomile Extract, PEG-120 Methyl Glucose Dioleate, Disodium EDTA, Citric Acid.